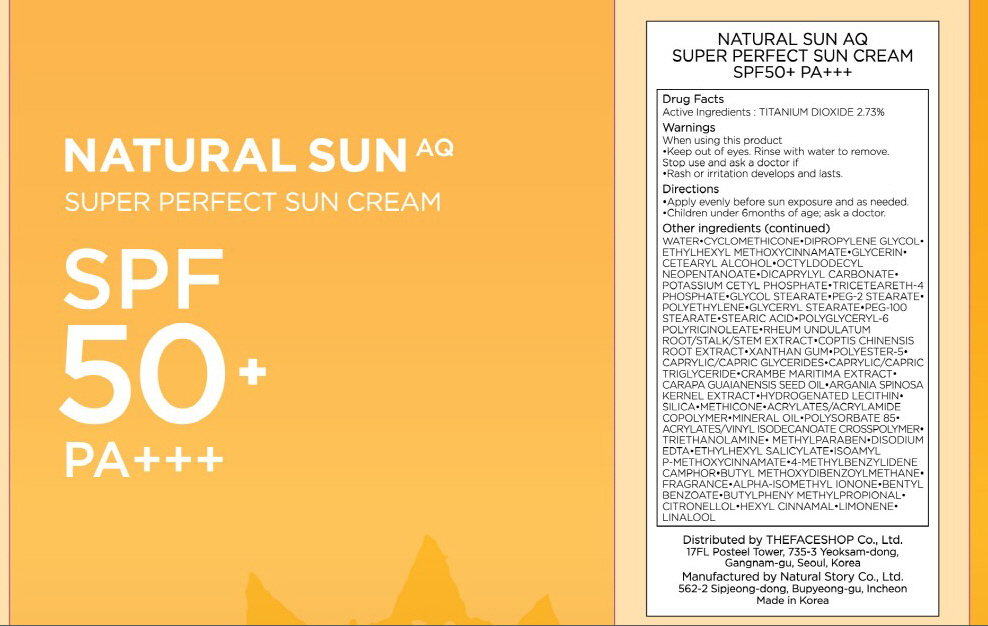 DRUG LABEL: NATURAL SUN AQ SUPER PERFECT SUN
NDC: 51523-021 | Form: CREAM
Manufacturer: THEFACESHOP CO., LTD.
Category: otc | Type: HUMAN OTC DRUG LABEL
Date: 20100714

ACTIVE INGREDIENTS: TITANIUM DIOXIDE 1.36 mL/50 mL

Drug Facts

Active Ingredient: TITANIUM DIOXIDE

Inactive Ingredients:
WATER, CYCLOMETHICONE, DIPROPYLENE GLYCOL, ETHYLHEXYL METHOXYCINNAMATE, GLYCERIN, CETEARYL ALCOHOL, OCTYLDODECYL NEOPENTANOATE, DICAPRYLYL CARBONATE, POTASSIUM CETYL PHOSPHATE, TRICETEARETH-4 PHOSPHATE, GLYCOL STEARATE, PEG-2 STEARATE, POLYETHYLENE, GLYCERYL STEARATE, PEG-100 STEARATE, STEARIC ACID, POLYGLYCERYL-6 POLYRICINOLEATE, RHEUM UNDULATUM ROOT/STALK/STEM EXTRACT, COPTIS CHINENSIS ROOT EXTRACT, XANTHAN GUM, POLYESTER-5, CAPRYLIC/CAPRIC GLYCERIDES, CAPRYLIC/CAPRIC TRIGLYCERIDE, CRAMBE MARITIMA EXTRACT, CARAPA GUAIANENSIS SEED OIL, ARGANIA SPINOSA KERNEL EXTRACT, HYDROGENATED LECITHIN, SILICA, METHICONE, ACRYLATES/ACRYLAMIDE COPOLYMER, MINERAL OIL, POLYSORBATE 85, ACRYLATES/VINYL ISODECANOATE CROSSPOLYMER, TRIETHANOLAMINE, METHYLPARABEN, DISODIUM EDTA, ETHYLHEXYL SALICYLATE, ISOAMYL-p METHOXYCINNAMATE, 4-METHYLBENZYLIDENE CAMPHOR, BUTYL METHOXYDIBENZOYLMETHANE, FRAGRANCE, ALPHA-ISOMETHYL IONONE, BENTYL BENZOATE, BUTYLPHENY METHYLPROPIONAL, CITRONELLOL, HEXYL CINNAMAL, LIMONENE, LINALOOL

Warnings:
When using this product
Keep out of eyes. Rinse with water to remove.
Stop use and ask a doctor if
Rash or irritation develops and lasts.
Directions:
Apply evenly before sun exposure and as needed.
Children under 6months of age; ask a doctor.